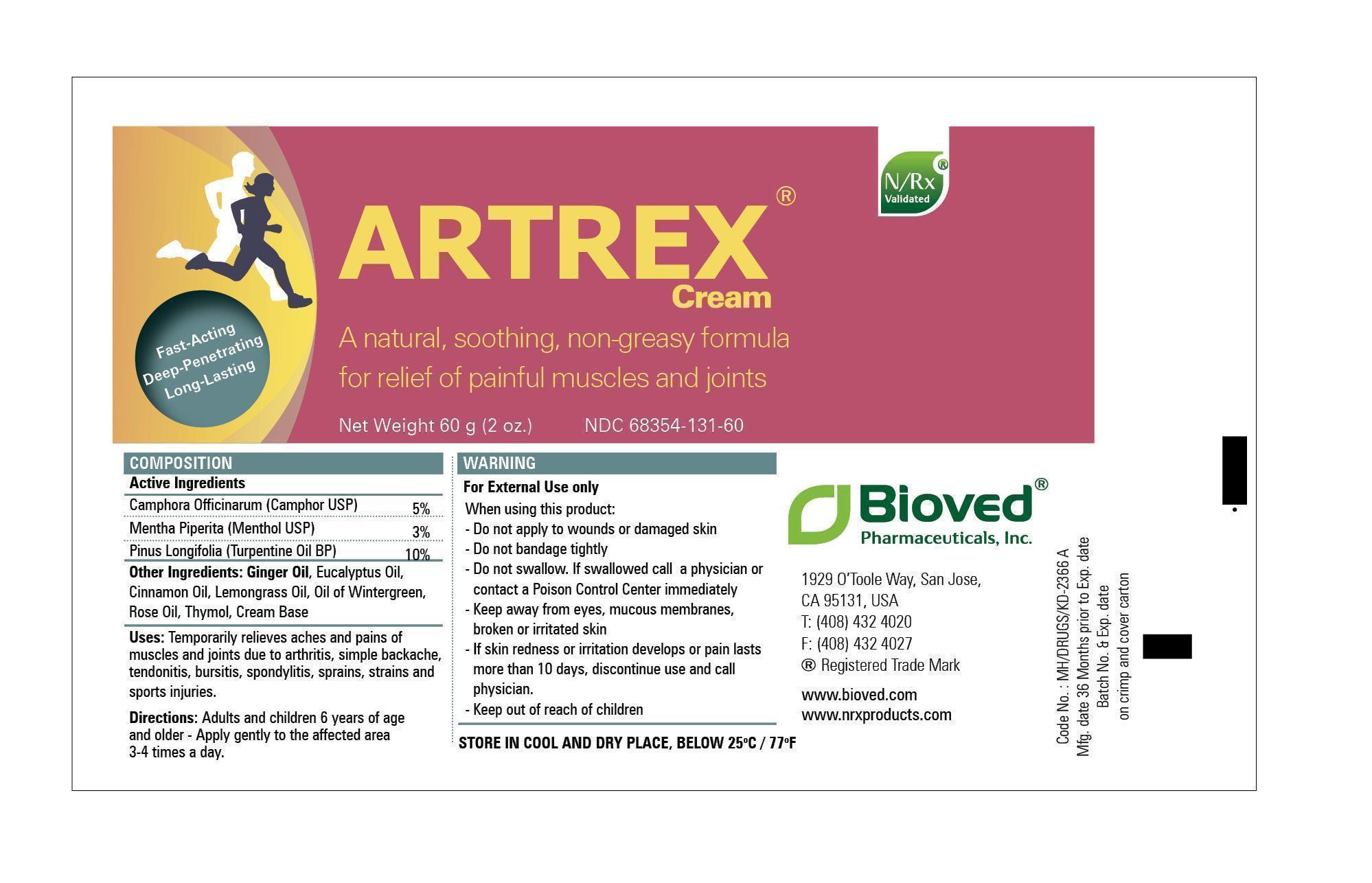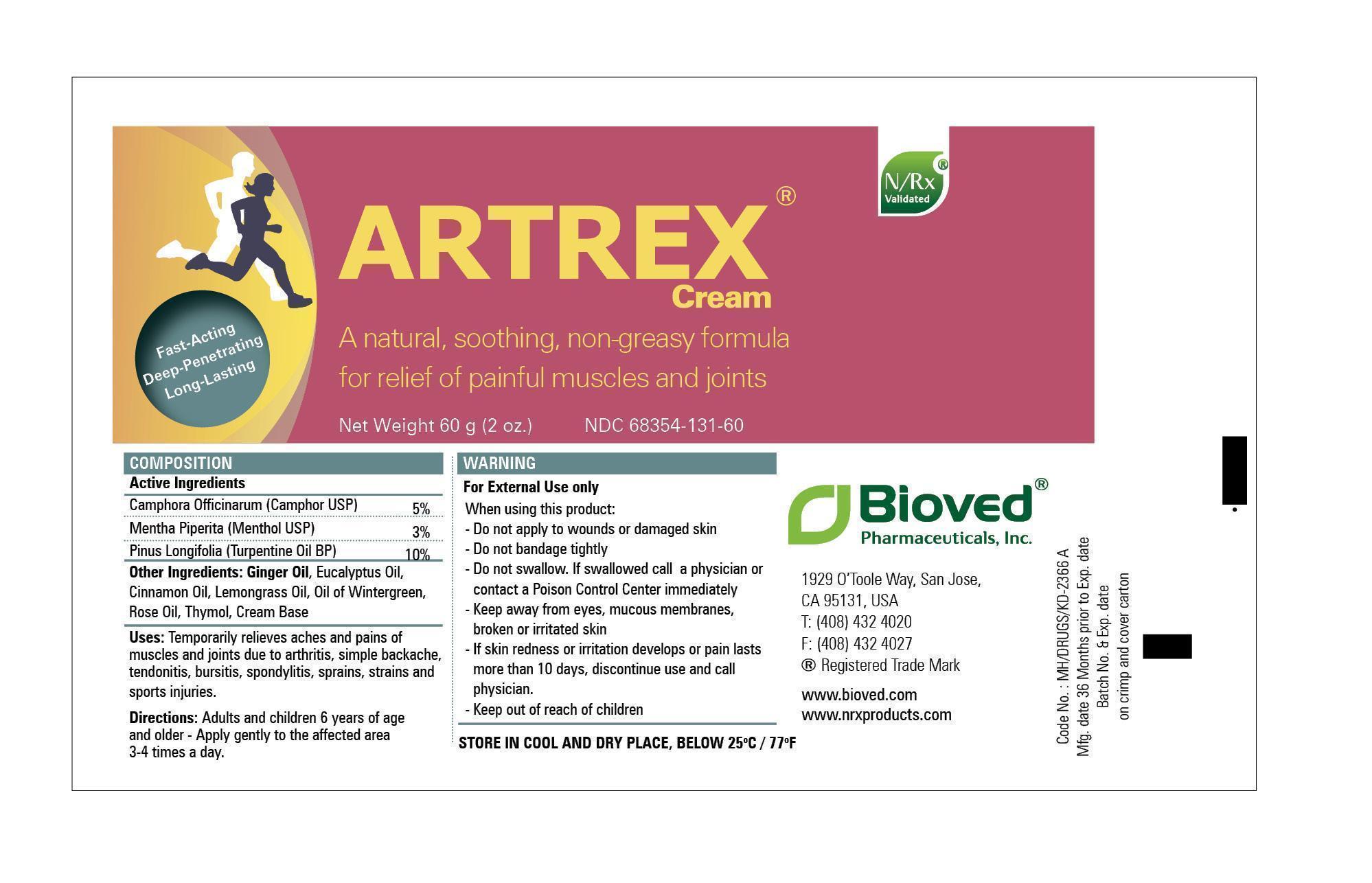 DRUG LABEL: ARTREX
NDC: 68354-131 | Form: CREAM
Manufacturer: Bioved Pharmaceuticals
Category: otc | Type: HUMAN OTC DRUG LABEL
Date: 20250410

ACTIVE INGREDIENTS: CAMPHOR (NATURAL) 3 g/60 g; MENTHOL 1.8 g/60 g; TURPENTINE 6 g/60 g
INACTIVE INGREDIENTS: METHYL SALICYLATE; EUCALYPTUS OIL; WEST INDIAN LEMONGRASS OIL; CINNAMON OIL; ROSE OIL; GINGER OIL; THYMOL

Composition

Active Ingredients:

Camphora Officinarum (Camphor) 5 %
Mentha Piperita (Menthol) 3 %
Pinus Longifolia(Turpentine Oil) 10 %

PURPOSE

Topical Analgesic

KEEP OUT OF REACH OF CHILDREN

INDICATIONS AND USAGE

Temporarily relieves aches and pains of muscles and joints due to arthritis, simple backache, sprains, strains,
and sports injuries

WARNINGS

- Do not apply to wound or damaged skin
- Do not bandage tightly
- Do not swallow. If swallowed call a physician or contact a poison control center immediately
- Keep away from eyes, mucous membranes, broken or irritated skin
- If skin redness or irritation develops or pain lasts more than 10 days, discontinue use and call a physician

INACTIVE INGREDIENT

Other Ingredients

Cinnamon Oil, Eucalyptus Oil, Ginger Oil, Lemon Grass Oil, Oil of Wintergreen,

Rose Oil, Thymol, Cream Base

DOSAGE AND ADMINISTRATION

Adults and children 6 years of age and older

Apply to affected area 3-4 times a day

Artrex 60g Tube

Artrex Tube